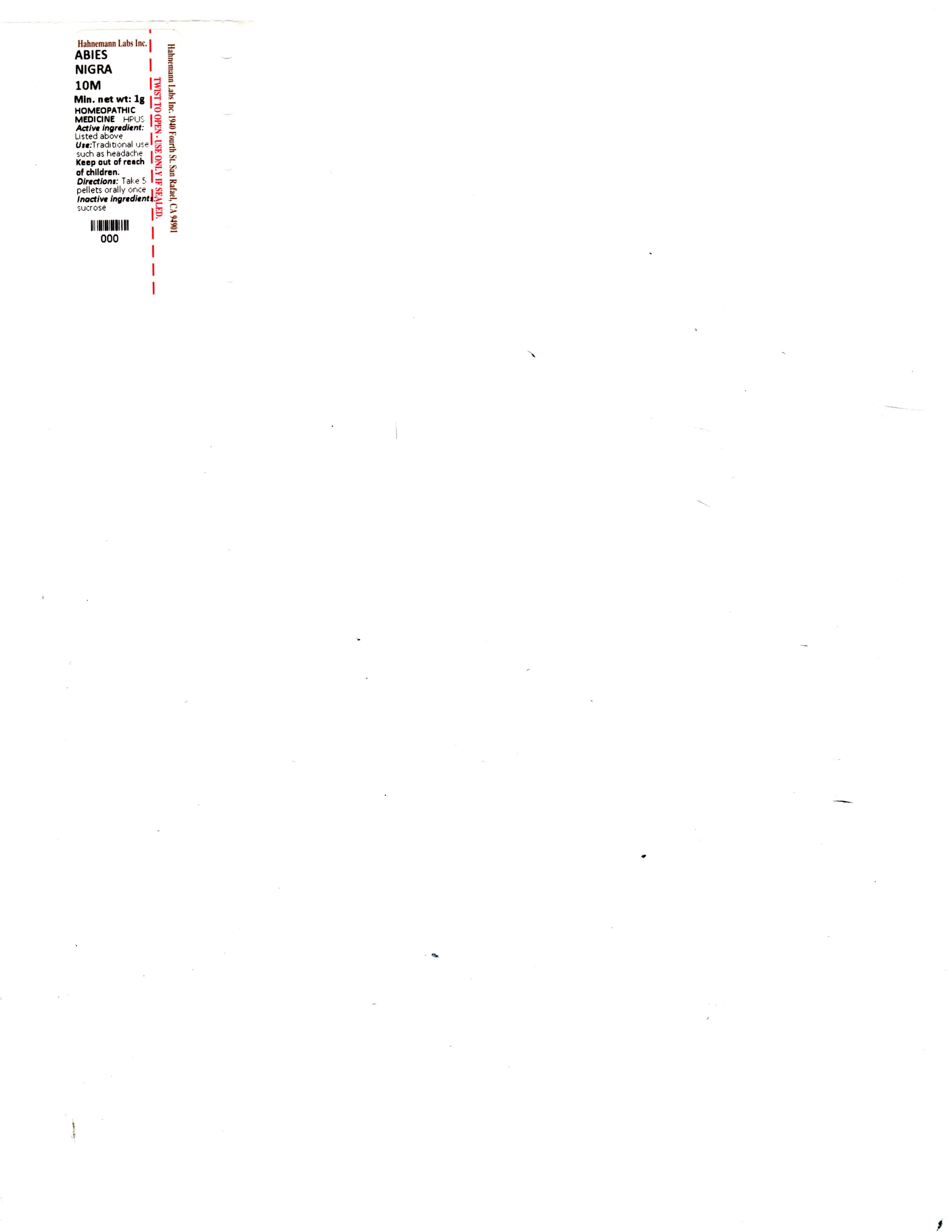 DRUG LABEL: Abies nigra
NDC: 63545-707 | Form: PELLET
Manufacturer: Hahnemann Laboratories, Inc.
Category: homeopathic | Type: HUMAN OTC DRUG LABEL
Date: 20250109

ACTIVE INGREDIENTS: PICEA MARIANA RESIN 10 [hp_M]/1 1
INACTIVE INGREDIENTS: SUCROSE

Single label image contains content for sections 1-15.

\